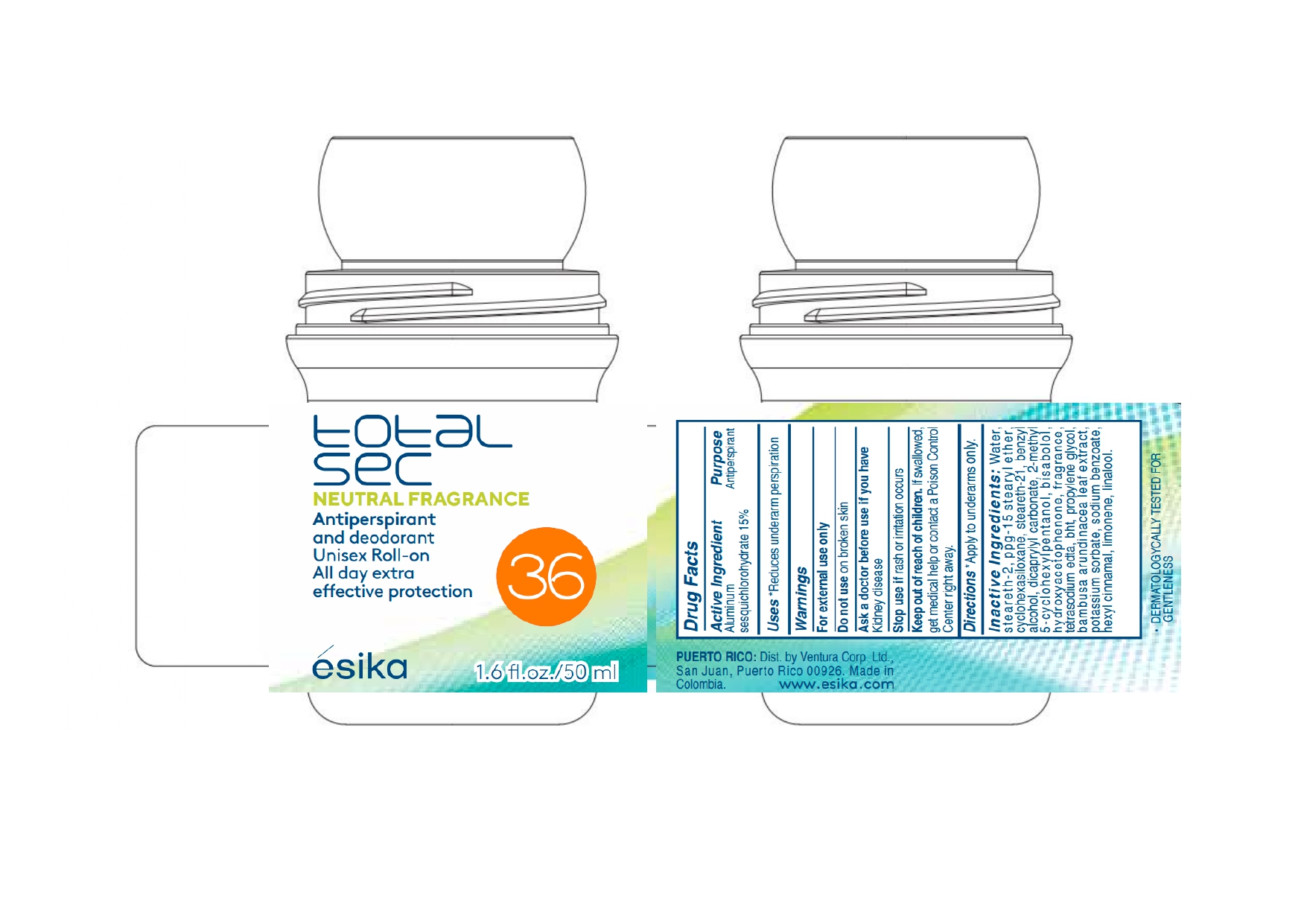 DRUG LABEL: esika total sec NEUTRAL FRAGRANCE Antiperspirant and deodorant Unisex Roll-on All day extra effective protection
NDC: 14141-962 | Form: EMULSION
Manufacturer: BEL STAR S A
Category: otc | Type: HUMAN OTC DRUG LABEL
Date: 20241028

ACTIVE INGREDIENTS: ALUMINUM SESQUICHLOROHYDRATE 15 g/100 mL
INACTIVE INGREDIENTS: PPG-15 STEARYL ETHER; CYCLOMETHICONE 6; PROPYLENE GLYCOL; WATER; 2-METHYL 5-CYCLOHEXYLPENTANOL; HYDROXYACETOPHENONE; EDETATE SODIUM; STEARETH-21; DICAPRYLYL CARBONATE; LEVOMENOL; BUTYLATED HYDROXYTOLUENE; .ALPHA.-HEXYLCINNAMALDEHYDE; POTASSIUM SORBATE; STEARETH-2; BENZYL ALCOHOL; SODIUM BENZOATE; LIMONENE, (+)-; LINALOOL, (+/-)-; BAMBUSA BAMBOS LEAF

esika total sec NEUTRAL FRAGRANCE Antiperspirant and deodorant Unisex Roll-on All day extra effective protection

Active Ingredient

Aluminum sesquichlorohydrate 15%

Purpose

Antiperspirant

Uses

Reduces underarm perspiration

Warnings

For external use only

Do not use

on broken skin

Ask a doctor before use if you have

Kidney disease

Stop use if

rash or irritation occurs

Keep out of reach of children.

If swallowed, get medical help or contact a Poison Control Center right away.

Directions

Apply to underarms only

Inactive ingredients

Water, steareth-2, ppg-15 stearyl ether, cyclohexasiloxane, steareth-21, benzyl alcohol, dicaprylyl carbonate, 2-methyl 5-cyclohexylpentanol, bisabolol, hydroxyacetophenone, fragrance, tetrasodium edta, bht, propylene glycol, bambusa arundinacea leaf extract, potassium sorbate, sodium benzoate, hexyl cinnamal, limonene, linalool.

Product Packaging

total sec

NEUTRAL FRAGRANCE

Antiperspirant and deodorant

Unisex roll-on

All day extra effective protection

esika

1.6 fl. oz./50 ml